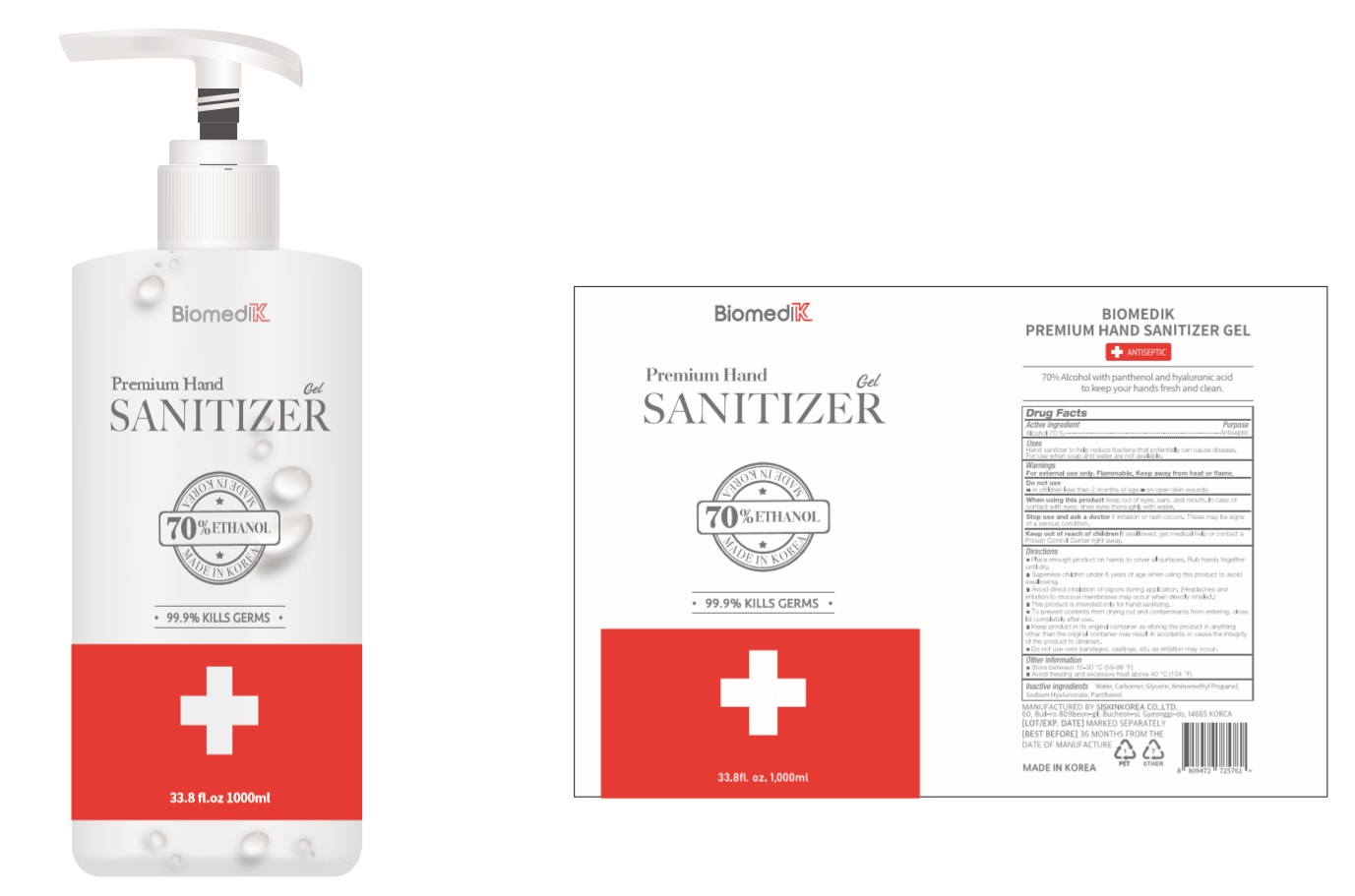 DRUG LABEL: BIOMEDIK Premium HAND SANITIZER Gel
NDC: 74514-1000 | Form: GEL
Manufacturer: SISKINKOREA CO.,LTD.
Category: otc | Type: HUMAN OTC DRUG LABEL
Date: 20200602

ACTIVE INGREDIENTS: ALCOHOL 700 mL/1000 mL
INACTIVE INGREDIENTS: GLYCERIN; AMINOMETHYLPROPANOL; PANTHENOL; WATER; HYALURONATE SODIUM; CARBOMER HOMOPOLYMER, UNSPECIFIED TYPE

BIOMEDIK Premium Hand Sanitizer Gel [74514-1000-1] 1000 mL, Bottle+Pump